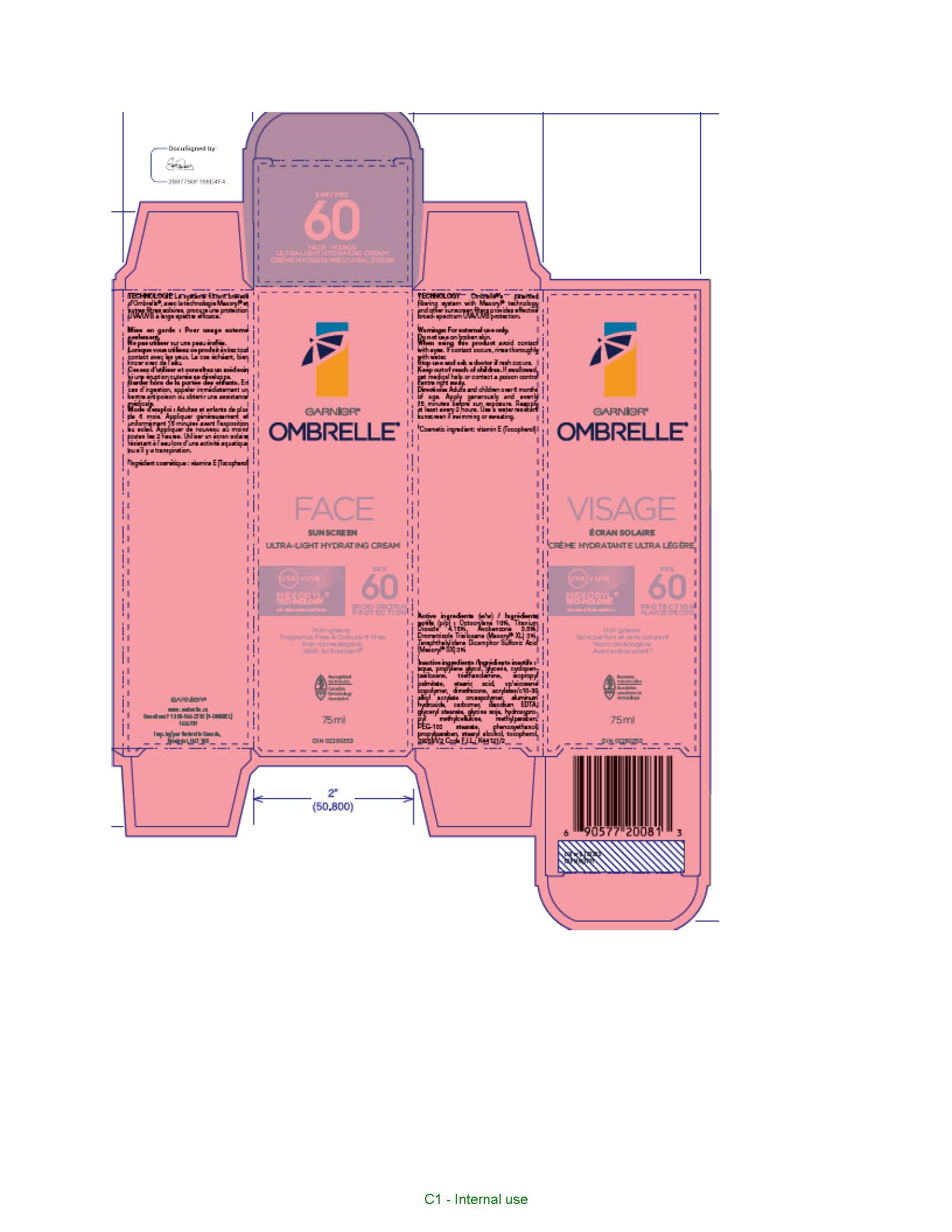 DRUG LABEL: Garnier Ombrelle Ultra Light Hydrating Face Sunscreen
NDC: 49967-200 | Form: LOTION
Manufacturer: L'OREAL USA PRODUCTS INC
Category: otc | Type: HUMAN OTC DRUG LABEL
Date: 20260107

ACTIVE INGREDIENTS: AVOBENZONE 35 mg/1 mL; DROMETRIZOLE TRISILOXANE 30 mg/1 mL; OCTOCRYLENE 100 mg/1 mL; TITANIUM DIOXIDE 41.5 mg/1 mL
INACTIVE INGREDIENTS: WATER; PROPYLENE GLYCOL; GLYCERIN; TROLAMINE; ISOPROPYL PALMITATE; STEARIC ACID; EICOSYL POVIDONE; DIMETHICONE; CARBOMER INTERPOLYMER TYPE A (ALLYL SUCROSE CROSSLINKED); ALUMINUM HYDROXIDE; CARBOMER HOMOPOLYMER, UNSPECIFIED TYPE; EDETATE DISODIUM; GLYCERYL MONOSTEARATE; SOYBEAN; HYPROMELLOSE, UNSPECIFIED; METHYLPARABEN; PEG-100 STEARATE; PHENOXYETHANOL; PROPYLPARABEN; STEARYL ALCOHOL; TOCOPHEROL

Drug Facts

Active ingredients

Avobenzone 3.5%
Octocrylene 10%
Drometrizole Trisiloxane 3%
Titanium Dioxide 4.15%

Warnings

For external use only. When using this product avoid contact with eyes. If contact occurs, rinse thoroughlly with water. Do not use on broken skin. Stop use and ask a doctor if rash occurs. Keep out of reach of children. If swallowed get medical help or contact a poison control center right away.

Directions

Adults and children over 6 months and up. Apply generously and evenly 15 minutes before sun exposure. Reapply at least every 2 hours, use a water resistant sunscreen if swimming or sweating.

Inactive ingredients

water, propylene glycol, glycerin, cyclopentasiloxane, triethanolamine, isoproypl palmitate, stearic acid, VP/eicosene copolymer, dimethicone, acrylates/c10-30 alkyl acrylate crosspolyer, aluminum hydroxide, carbomer, disodium EDTA, glyceryl stearate, glycine soja, hydroxypropyl methylcellulose, methylparaben, PEG-100 stearate, phenoxyethanol, propylparaben, stearyl alcohol, tocopherol